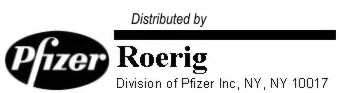 DRUG LABEL: Unknown
Manufacturer: Roerig
Category: prescription | Type: HUMAN PRESCRIPTION DRUG LABELING
Date: 20051214

UROBIOTIC®-250
CAPSULES

Each capsule contains

Oxytetracycline hydrochloride equivalent to. . . . . . . . . . . . . . . . . . . . . . . . . . . . . . . 250 mg
oxytetracycline

Sulfamethizole . . . . . . . . . . . . . . . . . . . . . . . . . . . . . . . . . . . . . . . . . . . . . . . . . . . . . . . 250 mg

Phenazopyridine hydrochloride . . . . . . . . . . . . . . . . . . . . . . . . . . . . . . . . . . . . . . . . . . . 50 mg

Inert ingredients in the formulation are: hard gelatin capsules (which may contain Green 3, Yellow 6, Yellow 10 and other inert ingredients); magnesium stearate; sodium lauryl sulfate; starch.

ACTIONS

Urobiotic-250 is a product designed for use specifically in urinary tract infections.

Terramycin® (oxytetracycline HCl) is a widely used antibiotic with clinically proved activity against gram-positive and gram-negative bacteria, rickettsiae, spirochetes, large viruses, and certain protozoa. Terramycin is well tolerated and well absorbed after oral administration. It diffuses readily through the placenta and is present in the fetal circulation. It diffuses into the pleural fluid, and under some circumstances, into the cerebrospinal fluid. Oxytetracycline HCl appears to be concentrated in the hepatic system and is excreted in the bile. It is excreted in the urine and in the feces, in high concentrations, in a biologically active form.

Sulfamethizole is a chemotherapeutic agent active against a number of important gram-positive and gram-negative bacteria. This sulfonamide is well absorbed, has a low degree of acetylation, and is extremely soluble. Because of these features and its rapid renal excretion, sulfamethizole has a low order of toxicity and provides prompt and high concentrations of the active drug in the urinary tract.

Phenazopyridine is an orally absorbed agent which produces prompt and effective local analgesia and relief of urinary symptoms by virtue of its rapid excretion in the urinary tract. These effects are confined to the genitourinary system and are not accompanied by generalized sedation or narcosis.

INDICATIONS

Based on a review of this drug by the National Academy of Sciences-National Research Council and/or other information, FDA has classified the indications as follows:

"Lacking substantial evidence of effectiveness as a fixed combination":

Urobiotic-250 is indicated in the therapy of a number of genitourinary infections caused by susceptible organisms. These infections include the following: pyelonephritis, pyelitis, ureteritis, cystitis, prostatitis, and urethritis.

Since both Terramycin and sulfamethizole provide effective levels in blood, tissue, and urine, Urobiotic-250 provides a multiple antimicrobial approach at the site of infection. Both antibacterial components are active against the most common urinary pathogens, including Escherichia coli, Pseudomonas aeruginosa, Aerobacter aerogenes, Streptococcus faecalis, Streptococcus hemolyticus, and Micrococcus pyogenes. Urobiotic-250 is particularly useful in the treatment of infections caused by bacteria more sensitive to the combination than to either component alone. The combination is also of value in those cases with mixed infections, and in those instances where the causative organism is unknown pending laboratory isolation.

Final classification of the less than effective indications requires further investigation. Clinical studies to substantiate the efficacy of Urobiotic 250 are ongoing. Completion of these ongoing studies will provide data for final classification of these indications.

CONTRAINDICATIONS

This drug is contraindicated in individuals who have shown hypersensitivity to any of its components.

This drug, because of the sulfonamide component, should not be used in patients with a history of sulfonamide sensitivities, and in pregnant females at term.

WARNINGS

If renal impairment exists, even usual oral or parenteral doses may lead to excessive systemic accumulation of the drug and possible liver toxicity. Under such conditions, lower than usual doses are indicated and if therapy is prolonged, tetracycline serum level determinations may be advisable.

Oxytetracycline HCl, which is one of the ingredients of Urobiotic-250, may form a stable calcium complex in any bone-forming tissue with no serious harmful effects reported thus far in humans. However, use of oxytetracycline during tooth development (last trimester of pregnancy, neonatal period and early childhood) may cause discoloration of the teeth (yellow-grey-brownish). This effect occurs mostly during long term use of the drug but it also has been observed in usual short treatment courses.

Because of its sulfonamide content, this drug should be used only after critical appraisal in patients with liver damage, renal damage, urinary obstruction, or blood dyscrasias. Deaths have been reported from hypersensitivity reactions, agranulocytosis, aplastic anemia, and other blood dyscrasias associated with sulfonamide administration. When used intermittently, or for a prolonged period, blood counts and liver and kidney function tests should be performed.

Certain hypersensitive individuals may develop a photodynamic reaction precipitated by exposure to direct sunlight during the use of this drug. This reaction is usually of the photoallergic type which may also be produced by other tetracycline derivatives. Individuals with a history of photosensitivity reactions should be instructed to avoid exposure to direct sunlight while under treatment with this or other tetracycline drugs, and treatment should be discontinued at first evidence of skin discomfort.

NOTE: Reactions of a photoallergic nature are exceedingly rare with Terramycin (oxytetracycline HCl). Phototoxic reactions are not believed to occur with Terramycin.

PRECAUTIONS

As with all antibiotic preparations, use of this drug may result in overgrowth of nonsusceptible organisms, including fungi. If superinfection occurs, the antibiotic should be discontinued and appropriate specific therapy should be instituted. This drug should be used with caution in persons having histories of significant allergies and/or asthma.

ADVERSE REACTIONS

Glossitis, stomatitis, proctitis, nausea, diarrhea, vaginitis, and dermatitis, as well as reactions of an allergic nature, may occur during oxytetracycline HCl therapy, but are rare. If adverse reactions, individual idiosyncrasy, or allergy occur, discontinue medication. Rare instances of esophagitis and esophageal ulcerations have been reported in patients receiving capsule forms of drugs in the tetracycline class. Most of these patients took medications immediately before going to bed. (See Dosage and Administration.)

With oxytetracycline therapy bulging fontanels in infants and benign intracranial hypertension in adults have been reported in individuals receiving full therapeutic dosages. These conditions disappeared rapidly when the drug was discontinued.

As in all sulfonamide therapy, the following reactions may occur: nausea, vomiting, diarrhea, hepatitis, pancreatitis, blood dyscrasias, neuropathy, drug fever, skin rash, injection of the conjunctiva and sclera, petechiae, purpura, hematuria and crystalluria. The dosage should be decreased or the drug withdrawn, depending upon the severity of the reaction.

DOSAGE AND ADMINISTRATION

Urobiotic-250 is recommended in adults only. A dose of 1 capsule four times daily is suggested. In refractory cases 2 capsules four times a day may be used.

Therapy should be continued for a minimum of seven days or until bacteriologic cure in acute urinary tract infections.

Administration of adequate amounts of fluid along with capsule forms of drugs in the tetracycline class is recommended to wash down the drugs and reduce the risk of esophageal irritation and ulceration. (SeeAdverse Reactions.)

To aid absorption of the drug, it should be given at least one hour before or two hours after eating. Aluminum hydroxide gel given with antibiotics has been shown to decrease their absorption and is contraindicated.

SUPPLY

Urobiotic-250 capsules: bottles of 50 (NDC 0049-0920-50), and unit dose packages of 100 (10 × 10's) (NDC 0049-0920-41).

Rx only

70-1636-00-9
December 1986